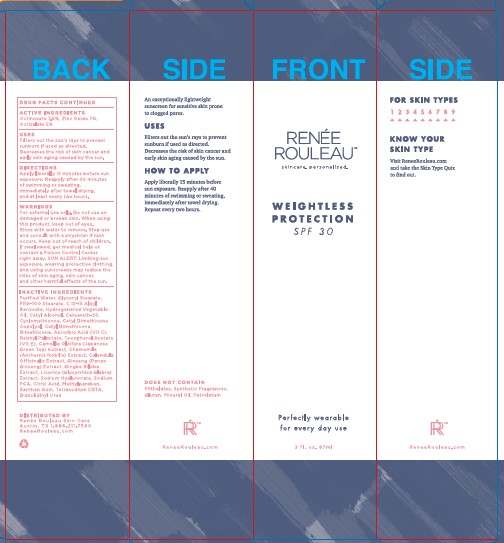 DRUG LABEL: WEIGHTLESS PROTECTION

NDC: 70712-102 | Form: LOTION
Manufacturer: Botanical Science Technologies
Category: otc | Type: HUMAN OTC DRUG LABEL
Date: 20251030

ACTIVE INGREDIENTS: OCTINOXATE 7.5 g/100 mL; ZINC OXIDE 7 g/100 mL; OCTISALATE 5 g/100 mL
INACTIVE INGREDIENTS: WATER; ALKYL (C12-15) BENZOATE; GLYCERYL MONOSTEARATE; CETYL ALCOHOL; HYDROGENATED COCONUT OIL; POLYOXYL 20 CETOSTEARYL ETHER; CYCLOMETHICONE; CETYL DIMETHICONE 45; ASCORBIC ACID; .ALPHA.-TOCOPHEROL ACETATE; CALENDULA OFFICINALIS WHOLE; CHAMAEMELUM NOBILE WHOLE; GINKGO BILOBA WHOLE; PEG-100 STEARATE; PANAX GINSENG WHOLE; GREEN TEA LEAF; GLYCYRRHIZA GLABRA; SODIUM PYRROLIDONE CARBOXYLATE; HYALURONATE SODIUM; XANTHAN GUM; VITAMIN A PALMITATE; ANHYDROUS CITRIC ACID; METHYLPARABEN; EDETATE SODIUM; DIAZOLIDINYL UREA

BOTANICAL SCIENCE - RENEE ROULEAU WEIGHTLESS PROTECTION SPF-30 (70712-102)

ACTIVE INGREDIENTS

OCTINOXATE 7.5%

ZINC OXIDE 7.0%

OCTISALATE 5.0%

PURPOSE

SUNSCREEN

USES

FILTERS OUT THE SUN'S RAYS TO PREVENT SUNBURN IF USED AS DIRECTED.

DECREASES THE RISK OF SKIN CANCER AND EARLY SKIN AGING CAUSED BY THE SUN.

WARNINGS

FOR EXTERNAL USE ONLY. DO NOT USE ON DAMAGED OR BROKEN SKIN. WHEN USING THIS PRODUCT, KEEP OUT OF EYES. RINSE WITH WATER TO REMOVE. STOP USE AND CONSULT WITH A PHYSICIAN IF RASH OCCURS. KEEP OUT OF REACH OF CHILDREN. IF SWALLOWED, GET MEDICAL HELP OR CONTACT A POISON CONTROL CENTER RIGHT AWAY. SUN ALERT: LIMITING SUN EXPOSURE AND USING SUNSCREENS MAY REDUCE THE RISKS OF SKIN AGING, SKIN CANCER, AND OTHER HARMFUL EFFECTS OF THE SUN.

DIRECTIONS

APPLY LIBERALLY 15 MINUTES BEFORE SUN EXPOSURE. REAPPLY AFTER 40 MINUTES OF SWIMMING OR SWEATING, IMMEDIATELY AFTER TOWEL DRYING, AND AT LEAST EVERY TWO HOURS.

Keep out of reach of children.

INACTIVE INGREDIENTS

PURIFIED WATER, GLYCERYL STEARATE, PEG-100 STEARATE, C12-15 ALKYL BENZOATE, HYDROGENATED VEGETABLE OIL, CETYL ALCOHOL, CETEARETH-20, CYCLOMETHICONE, CETYL DIMETHICONE COPOLYOL, CETYL DIMETHICONE, ASCORBIC ACID (VIT C), RETINYL PALMITATE, TOCOPHERYL ACETATE (VIT E), CAMELLIA OLEIFERA (JAPANESE GREEN TEA) EXTRACT, CHAMOMILE (ANTHEMIS NOBOLIS) EXTRACT, CALENDULA OFFICINALIS EXTRACT, GINSENG (PANAX GINSENG) EXTRACT, GINGKO BILOBA EXTRACT, LICORICE (GLYCYRRHIZA GLABRA) EXTRACT, SODIUM HYALURONATE, SODIUM PCA, CITRIC ACID, METHYLPARABEN, XANTHAN GUM, TETRASODIUM EDTA, DIAZOLIDINYL UREA